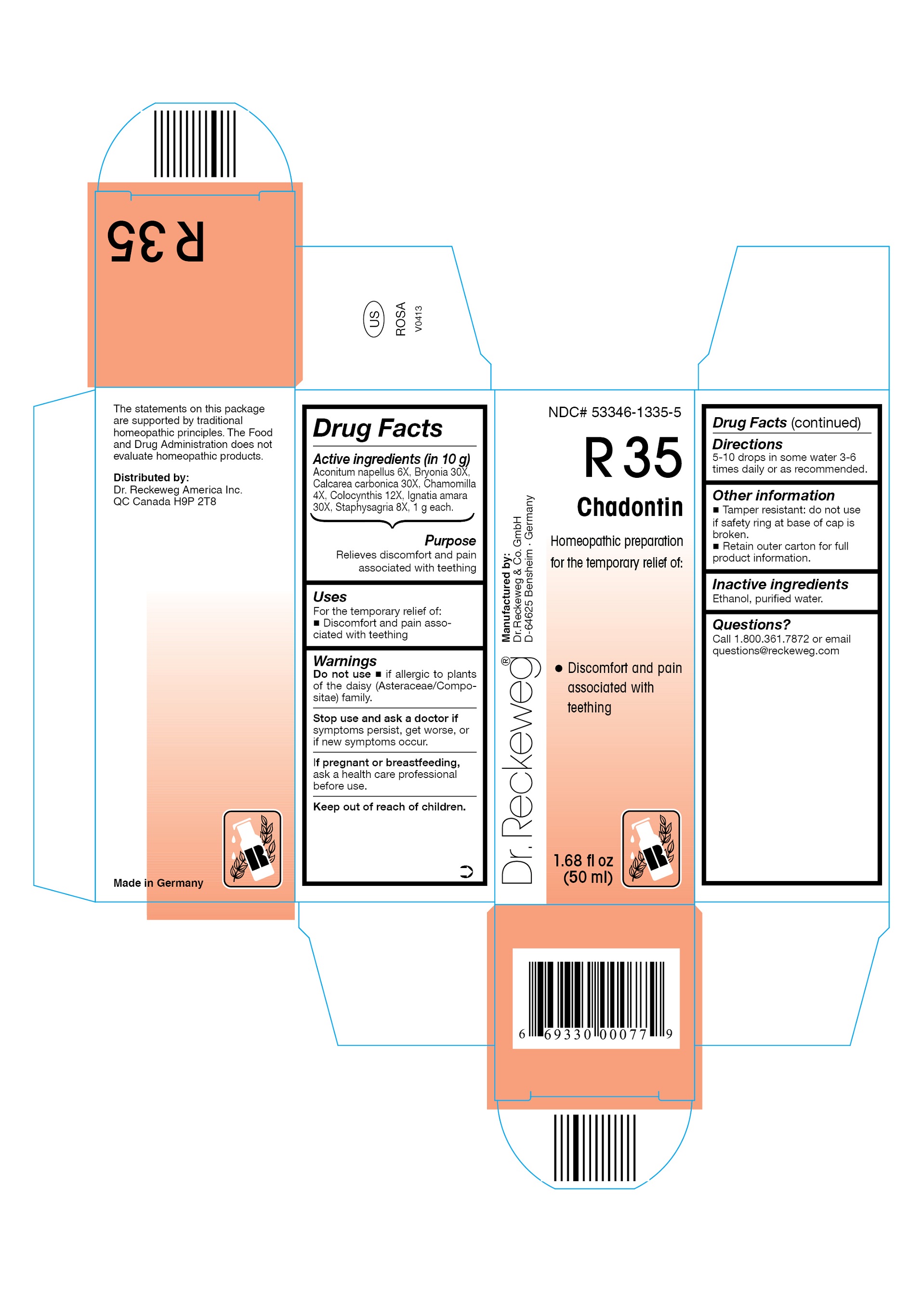 DRUG LABEL: DR. RECKEWEG R35 Chadontin
NDC: 53346-1335 | Form: LIQUID
Manufacturer: PHARMAZEUTISCHE FABRIK DR. RECKEWEG & CO
Category: homeopathic | Type: HUMAN OTC DRUG LABEL
Date: 20130404

ACTIVE INGREDIENTS: ACONITUM NAPELLUS 6 [hp_X]/50 mL; BRYONIA DIOICA ROOT 30 [hp_X]/50 mL; OYSTER SHELL CALCIUM CARBONATE, CRUDE 30 [hp_X]/50 mL; MATRICARIA RECUTITA 4 [hp_X]/50 mL; CITRULLUS COLOCYNTHIS FRUIT PULP 12 [hp_X]/50 mL; STRYCHNOS IGNATII SEED 30 [hp_X]/50 mL; DELPHINIUM STAPHISAGRIA SEED 8 [hp_X]/50 mL
INACTIVE INGREDIENTS: ALCOHOL; WATER

DR. RECKEWEG R35 Chadontin

Active ingredients

Aconitum napellus 6X, Bryonia 30X, Calcarea carbonica 30X, Chamomilla 4X, Colocynthis 12X, Ignatia amara 30X, Staphysagria 8X, 1 g each in 10 g.

Purpose

Relieves discomfort and pain associated with teething

Uses

For the temporary relief of:

- Discomfort and pain associated with teething

Warnings

Do not use

- if allergic to plants of the daisy (Asteraceae/Compositae) family.

Stop use and ask a doctor if symptoms persist, get worse, or if new symptoms occur.

PREGNANCY OR BREAST FEEDING

If pregnant or breastfeeding, ask a health care professional before use.

Keep out of reach of children.

Directions

5-10 drops in some water 3-6 times daily or as recommended.

Other information

- Tamper resistant: do not use if safety ring at base of cap is broken.
- Retain outer carton for full product information.

Inactive ingredients

Ethanol, purified water.

Questions?

Call 1-800-361-7872 or email questions@reckeweg.com

PACKAGE LABEL

NDC# 53346-1335-5

Dr. Reckeweg R35 Chadontin

Homeopathic preparation for the temporary relief of:

- Discomfort and pain associated with teething

Manufactured by:

Dr. Reckeweg Co. GmbH

D-64625 Bensheim

Germany

1.68 fl oz
(50 ml)